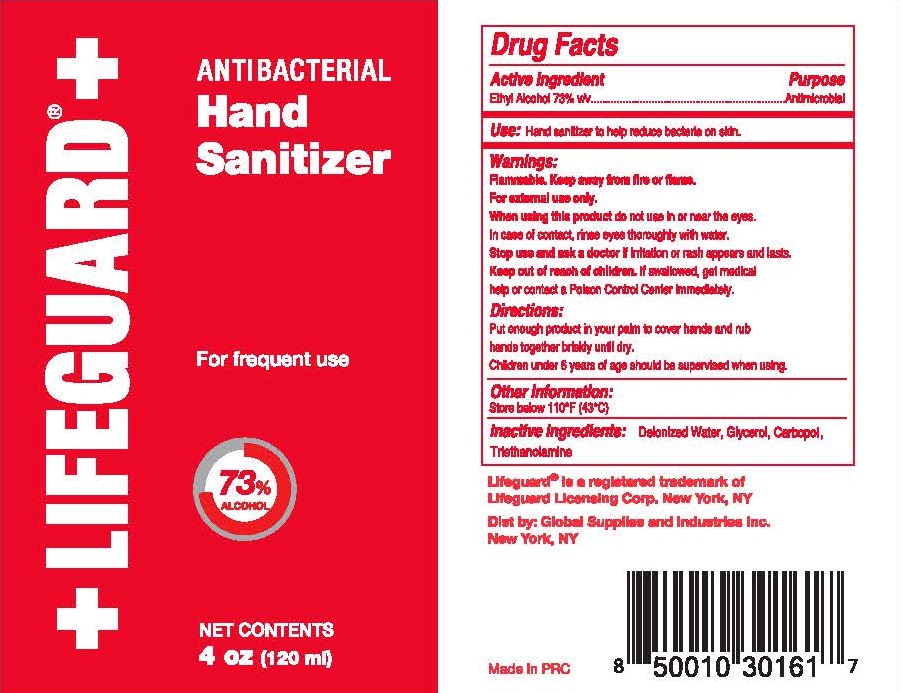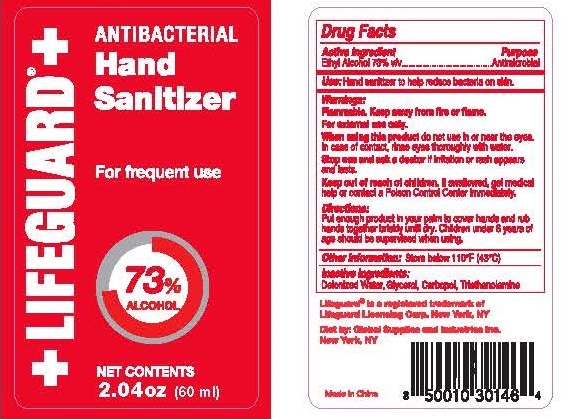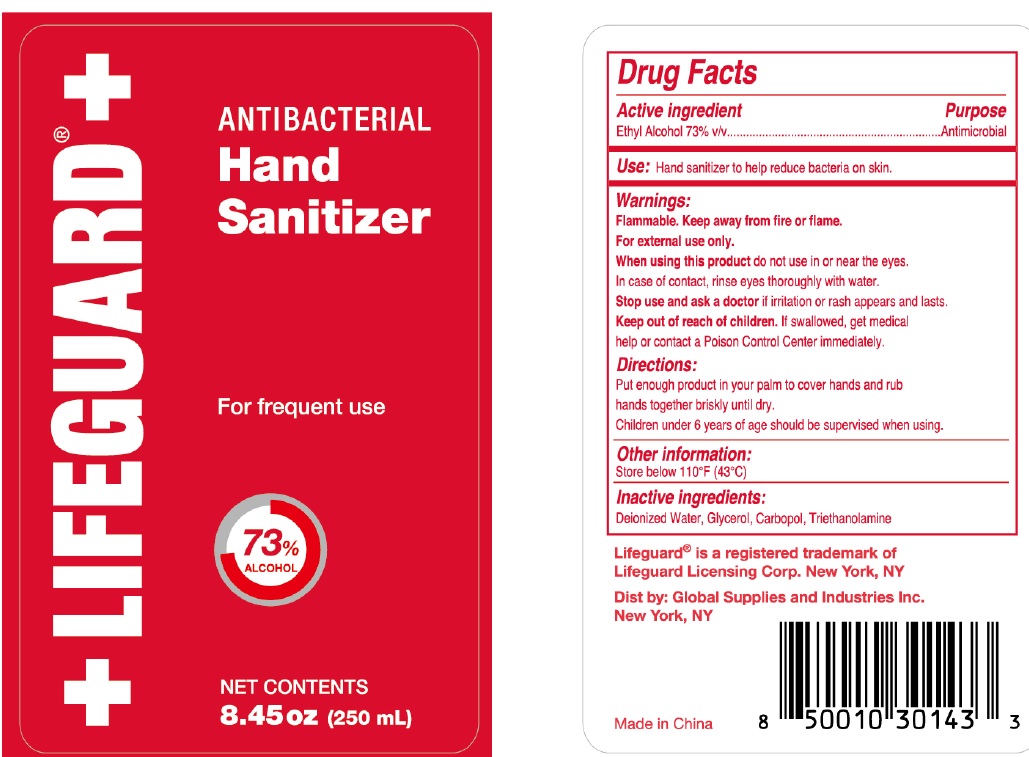 DRUG LABEL: Antibacterial Hand Sanitizer
NDC: 77879-001 | Form: LIQUID
Manufacturer: BT Supplies West Inc
Category: otc | Type: HUMAN OTC DRUG LABEL
Date: 20220209

ACTIVE INGREDIENTS: ALCOHOL 0.73 mL/1 mL
INACTIVE INGREDIENTS: WATER; GLYCERIN; CARBOMER HOMOPOLYMER, UNSPECIFIED TYPE; TROLAMINE

Antibacterial Hand Sanitizer

Active ingredient

Ethyl Alcohol 73% v/v

Purpose

Antimicrobial

Use:

Hand sanitizer to help reduce bacteria on skin.

Warnings:

Flammable. Keep away from fire or flame.
For external use only.

When using this product

do not use in or near the eyes. In case of contact, rinse eyes thoroughly with water

Stop use and ask a doctor

if irritation or rash appears and lasts.

Keep out of reach of children.

if swallowed, get medical help or contact a Poison Control Center immediately.

Directions:

Put enough product in your palm to cover hands and rub hands together briskly until dry.

Children under 6 years of age should be supervised when using

Other information:

Store below 110°F (43°C)

Inactive ingredients:

Deionized Water, Glycerol, Carbopol, Triethanolamine